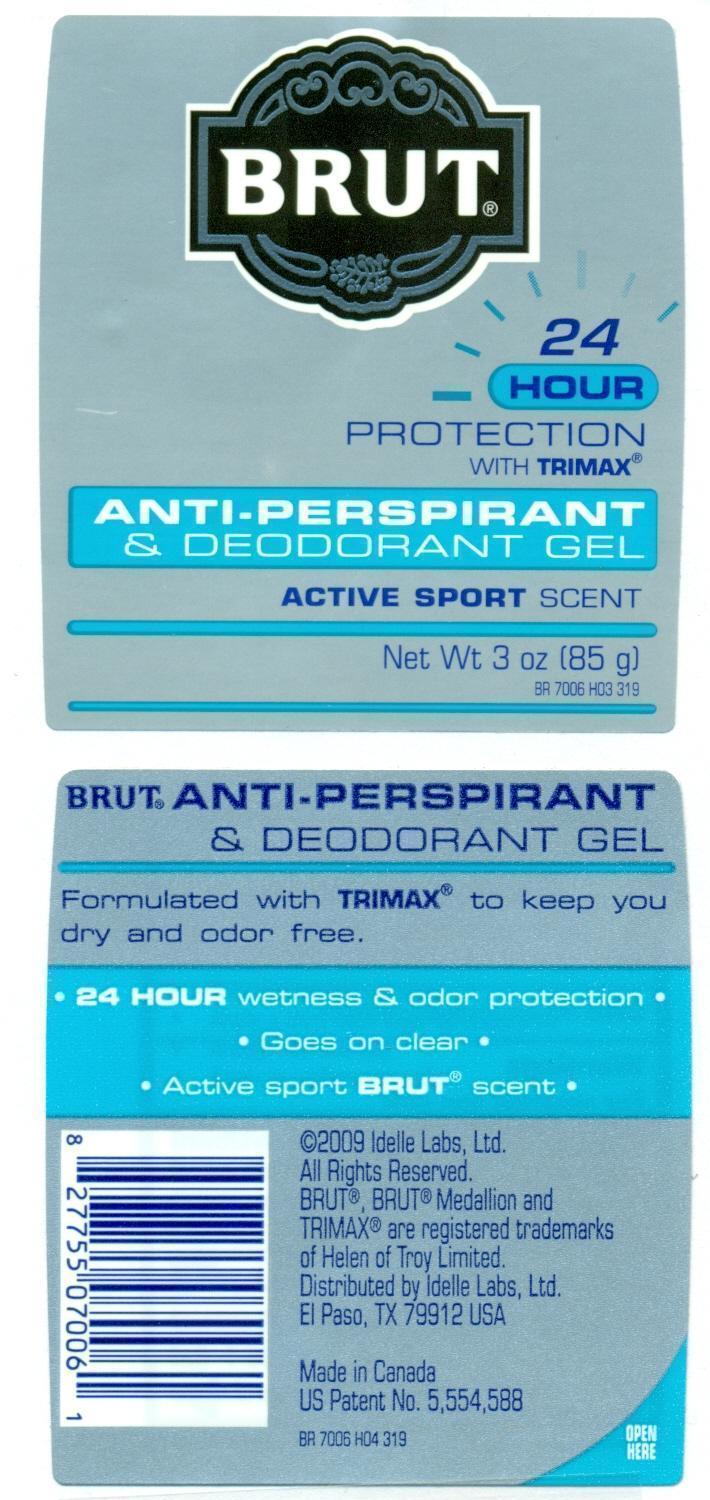 DRUG LABEL: BRUT Active Sport
NDC: 41595-7007 | Form: GEL
Manufacturer: Idelle Labs, Ltd
Category: otc | Type: HUMAN OTC DRUG LABEL
Date: 20130731

ACTIVE INGREDIENTS: ALUMINUM ZIRCONIUM TETRACHLOROHYDREX GLY 16.15 g/85 g
INACTIVE INGREDIENTS: CYCLOMETHICONE 5 5.27 g/85 g; DIMETHICONE 8.406 g/85 g; POLYETHYLENE GLYCOL 400 2.55 g/85 g; ALCOHOL 4.675 g/85 g; WATER 6.783 g/85 g

BRUT Active Sport

Active Ingredients:

Aluminum Zirconium Tetrachlorohydrex Gly (anhydrous)

Purpose:

Antiperspirant

Use:

Reduces underarm wetness.

Warning:

For external use only.

Stop use,

and ask a Doctor if rash or irritation develops.

Do not use on broken skin.

Keep out of reach of children.

In case of ingestion, get medial help or contact a Poison Control Center right away.

Directions:

Turn dial to raise product; Apply a thin, even layer to underarm; Always replace cap; Apply to underams only.

HOW SUPPLIED

2009 Idelle Labs, Ltd.

All Rights Reserved. BRUT, BRUT medallion and TRIMAX are registered trademarks of Helen of Troy Limited. Distributed by Idelle Labs, Ltd., El Paso, TX 79912, USA. Made in Canada.

QUESTIONS OR COMMENTS:

Call 1-800-487-7273